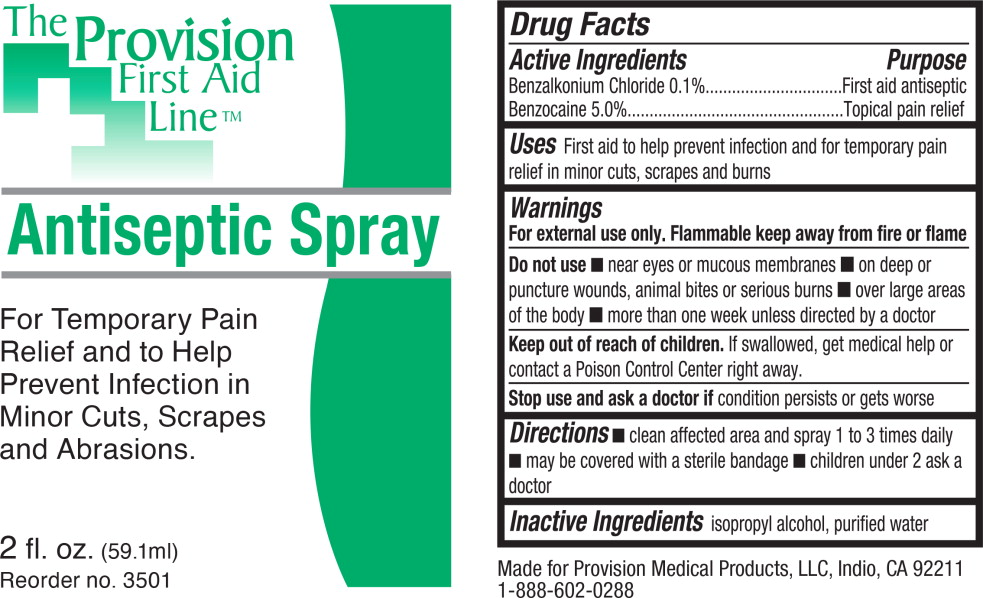 DRUG LABEL: Antiseptic
NDC: 69103-5300 | Form: SPRAY
Manufacturer: Provision Medical
Category: otc | Type: HUMAN OTC DRUG LABEL
Date: 20131111

ACTIVE INGREDIENTS: benzalkonium chloride 1 g/1 L; benzocaine 46 g/1 L
INACTIVE INGREDIENTS: isopropyl alcohol; water

Drug Facts

Active Ingredients

Benzalkonium Chloride 0.1%

Benzocaine 5.0%

Purpose

First aid antiseptic

Topical pain relief

Uses

First aid to help prevent infection and for temporary pain relief in minor cuts, scrapes and burns

Warnings

For external use only. Flammable keep away from fire or flame

Do not use

- near eyes or mucous membranes
- on deep or puncture wounds, animal bites or serious burns
- over large areas of the body
- more than one week unless directed by a doctor

Keep out of reach of children. If swallowed, get medical help or contact a Poison Control Center right away.

Stop use and ask a doctor if condition persists or gets worse

Directions

- clean affected area and spray 1 to 3 times daily
- may be covered with a sterile bandage
- children under 2 ask a doctor

Inactive Ingredients

isopropyl alcohol, purified water

Principal Display Panel – 2 fl. oz Packet Label

The Provision
First Aid
Line™

Antiseptic Spray

For Temporary Pain
Relief and to Help
Prevent Infection in
Minor Cuts, Scrapes
and Abrasions.

2 fl. oz. (59.1 ml)

Reorder no. 3501